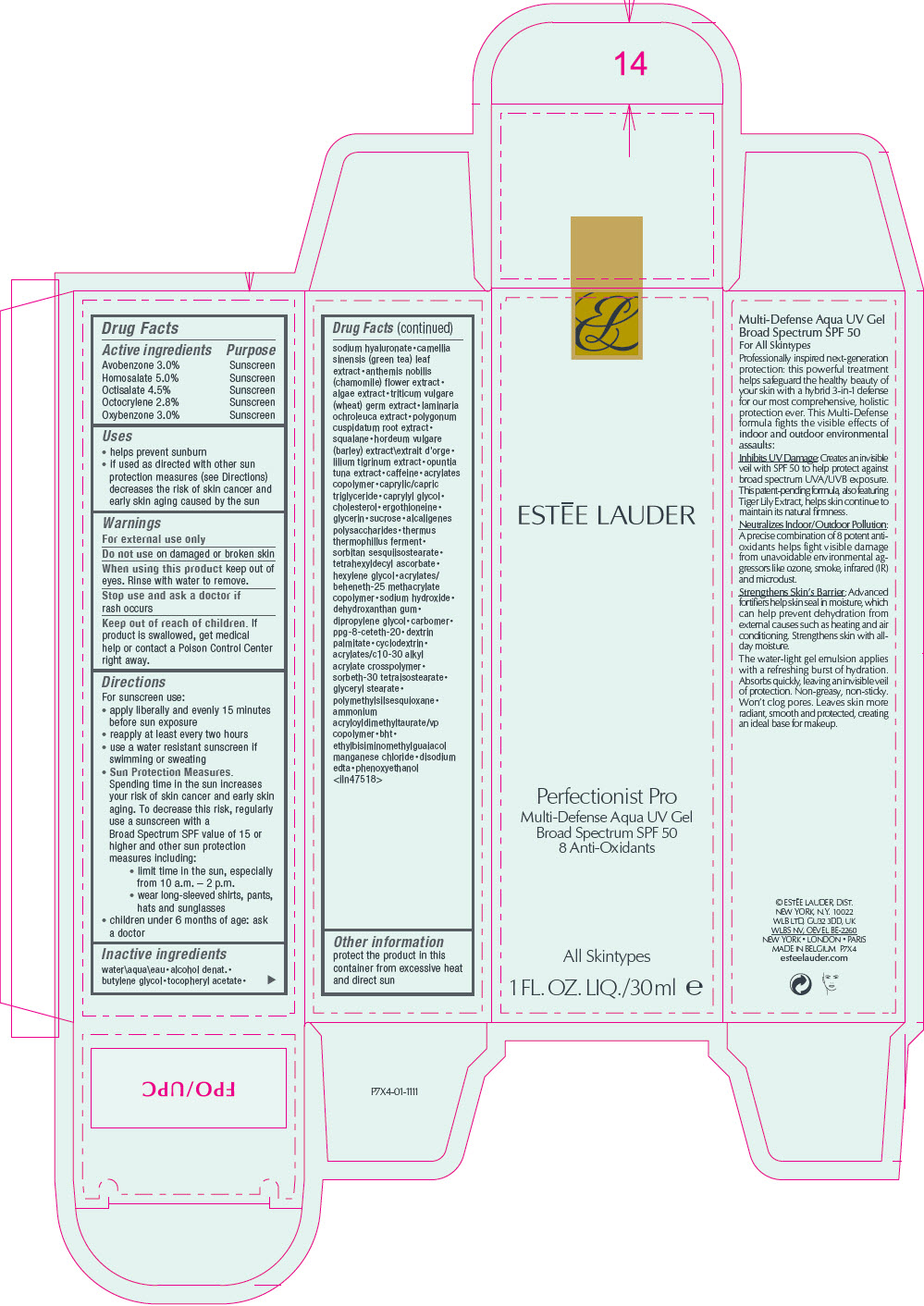 DRUG LABEL: ESTEE LAUDER MULTI-DEFENSE AQUA UV gel BROAD SPECTRUM SPF 50
NDC: 11559-060 | Form: LOTION
Manufacturer: ESTEE LAUDER INC
Category: otc | Type: HUMAN OTC DRUG LABEL
Date: 20241225

ACTIVE INGREDIENTS: AVOBENZONE 30 mg/1 mL; HOMOSALATE 50 mg/1 mL; OCTISALATE 45 mg/1 mL; OCTOCRYLENE 28 mg/1 mL; OXYBENZONE 30 mg/1 mL
INACTIVE INGREDIENTS: BUTYLATED HYDROXYTOLUENE; ETHYLBISIMINOMETHYLGUAIACOL MANGANESE CHLORIDE; EDETATE DISODIUM ANHYDROUS; PHENOXYETHANOL; WATER; ALCOHOL; 1,2-BUTANEDIOL; .ALPHA.-TOCOPHEROL ACETATE; HYALURONATE SODIUM; GREEN TEA LEAF; CHAMAEMELUM NOBILE FLOWER; SARGASSUM FILIPENDULA; WHEAT GERM; LAMINARIA OCHROLEUCA; REYNOUTRIA JAPONICA ROOT; SQUALANE; HORDEUM VULGARE ROOT; LILIUM LANCIFOLIUM BULB; OPUNTIA TUNA WHOLE; CAFFEINE; BUTYL ACRYLATE/METHYL METHACRYLATE/METHACRYLIC ACID COPOLYMER (18000 MW); MEDIUM-CHAIN TRIGLYCERIDES; CAPRYLYL GLYCOL; CHOLESTEROL; ERGOTHIONEINE; GLYCERIN; SUCROSE; ALCALIGENES FAECALIS; THERMUS THERMOPHILUS LYSATE; SORBITAN SESQUIISOSTEARATE; TETRAHEXYLDECYL ASCORBATE; HEXYLENE GLYCOL; BEHENETH-25 METHACRYLATE; SODIUM HYDROXIDE; DEHYDROXANTHAN GUM; DIPROPYLENE GLYCOL; CARBOMER HOMOPOLYMER, UNSPECIFIED TYPE; PPG-2-CETETH-9; DEXTRIN PALMITATE (CORN; 20000 MW); BETADEX; CARBOMER INTERPOLYMER TYPE A (ALLYL SUCROSE CROSSLINKED); PEG-10 SORBITAN LAURATE; GLYCERYL MONOSTEARATE; POLYMETHYLSILSESQUIOXANE (4.5 MICRONS); AMMONIUM ACRYLOYLDIMETHYLTAURATE/VP COPOLYMER

ESTĒE LAUDER MULTI-DEFENSE AQUA UV GEL BROAD SPECTRUM SPF 50

Drug Facts

ACTIVE INGREDIENT

Active ingredients | Purpose
Avobenzone 3.0% | Sunscreen
Homosalate 5.0% | Sunscreen
Octisalate 4.5% | Sunscreen
Octocrylene 2.8% | Sunscreen
Oxybenzone 3.0% | Sunscreen

Uses

- helps prevent sunburn
- if used as directed with other sun protection measures (see Directions) decreases the risk of skin cancer and early skin aging caused by the sun

Warnings

For external use only

Do not use on damaged or broken skin

When using this product keep out of eyes. Rinse with water to remove.

Stop use and ask a doctor if rash occurs

Keep out of reach of children. If product is swallowed, get medical help or contact a Poison Control Center right away.

Directions

For sunscreen use:

- apply liberally and evenly 15 minutes before sun exposure
- reapply at least every two hours
- use a water resistant sunscreen if swimming or sweating
- Sun Protection Measures.
  Spending time in the sun increases your risk of skin cancer and early skin aging. To decrease this risk, regularly use a sunscreen with a Broad Spectrum SPF value of 15 or higher and other sun protection measures including:
  - limit time in the sun, especially from 10 a.m. – 2 p.m.
  - wear long-sleeved shirts, pants, hats and sunglasses
- children under 6 months of age: ask a doctor

Inactive ingredients

water\aqua\eau • alcohol denat. • butylene glycol • tocopheryl acetate • sodium hyaluronate • camellia sinensis (green tea) leaf extract • anthemis nobilis (chamomile) flower extract • algae extract • triticum vulgare (wheat) germ extract • laminaria ochroleuca extract • polygonum cuspidatum root extract • squalane • hordeum vulgare (barley) extract\extrait d'orge • lilium tigrinum extract • opuntia tuna extract • caffeine • acrylates copolymer • caprylic/capric triglyceride • caprylyl glycol • cholesterol • ergothioneine • glycerin • sucrose • alcaligenes polysaccharides • thermus thermophillus ferment • sorbitan sesquiisostearate • tetrahexyldecyl ascorbate • hexylene glycol • acrylates/ beheneth-25 methacrylate copolymer • sodium hydroxide • dehydroxanthan gum • dipropylene glycol • carbomer • ppg-8-ceteth-20 • dextrin palmitate • cyclodextrin • acrylates/c10-30 alkyl acrylate crosspolymer • sorbeth-30 tetraisostearate • glyceryl stearate • polymethylsilsesquioxane • ammonium acryloyldimethyltaurate/vp copolymer • bht • ethylbisiminomethylguaiacol manganese chloride • disodium edta • phenoxyethanol
<iln47518>

Other information

protect the product in this container from excessive heat and direct sun

PRINCIPAL DISPLAY PANEL - 30 ml Tube Carton

ESTĒE LAUDER

Perfectionist Pro
Multi-Defense Aqua UV Gel
Broad Spectrum SPF 50
8 Anti-Oxidants

All Skintypes

1 FL. OZ. LIQ./30 ml e